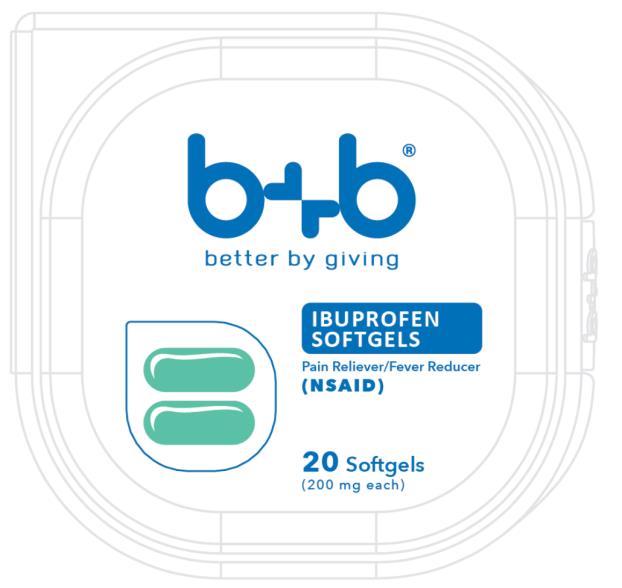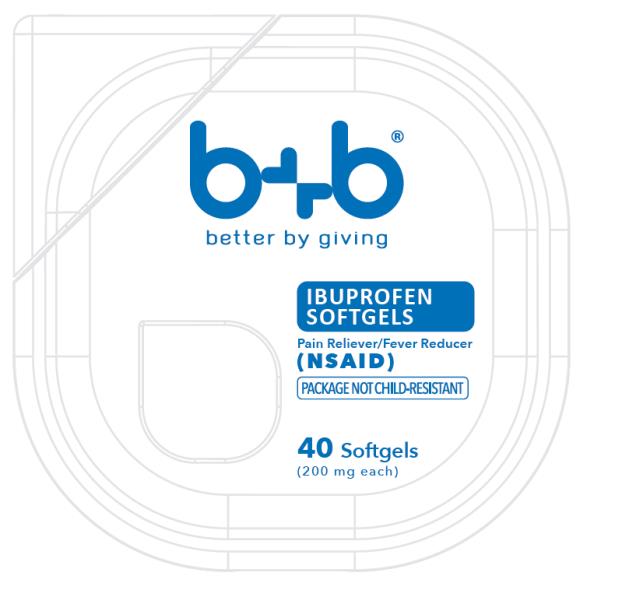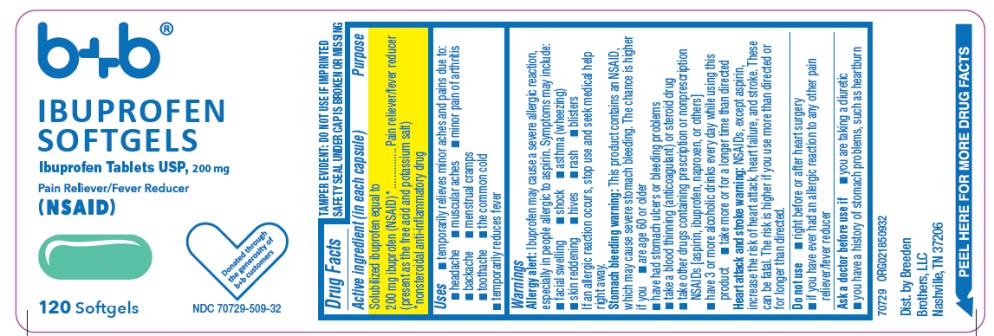 DRUG LABEL: Ibuprofen Softgels
NDC: 70729-000 | Form: CAPSULE
Manufacturer: Breeden Brothers, LLC
Category: otc | Type: HUMAN OTC DRUG LABEL
Date: 20180101

ACTIVE INGREDIENTS: IBUPROFEN 200 mg/1 1
INACTIVE INGREDIENTS: FD&C GREEN NO. 3; GELATIN; ISOPROPYL ALCOHOL; MEDIUM-CHAIN TRIGLYCERIDES; POLYETHYLENE GLYCOLS; POTASSIUM HYDROXIDE; WATER; SORBITOL

Ibuprofen Softgels

Drug Facts

Active ingredient (in each capsule)

Solubilized ibuprofen equal to Pain reliever/ 200 mg ibuprofen (NSAID)*

*nonsteroidal anti-inflammatory drug

Purpose

fever reducer (present as the free acid and potassium salt)

Drug Facts (continued)

Uses

_ temporarily relieves minor aches and pains due to:

_ muscular aches

_ the common cold

_ headache

_ toothache

_ backache

_ menstrual cramps

_ minor pain of arthritis

_ temporarily reduces fever

Warnings

Allergy alert: Ibuprofen may cause a severe allergic reaction, especially in people allergic to aspirin. Symptoms may include:

_ blisters

_ rash

_ hives

_ asthma (wheezing)

_ shock

_ skin reddening

_ facial swelling

If an allergic reaction occurs, stop use and seek medical help right away.

Stomach bleeding warning: This product contains an NSAID, which may cause severe stomach bleeding. The chance is higher if you:

_ take a blood thinning (anticoagulant) or

Drug Facts (continued)

steroid drug

_ are age 60 or older

_ have had stomach ulcers or bleeding problems

_ take other drugs containing prescription or nonprescription NSAIDs [aspirin, ibuprofen, naproxen, or others]

_ have 3 or more alcoholic drinks every day while using this product

_ take more or for a longer time than directed

Do not use

_ if you have ever had an allergic reaction to any other pain reliever/fever reducer

_ right before or after heart surgery

Ask a doctor before use if

_ stomach bleeding warning applies to you

_ you have a history of stomach problems, such as heartburn

_ you are taking a diuretic

Drug Facts (continued)

_ you have high blood pressure, heart disease, liver cirrhosis, kidney disease or asthma

_ you have problems or serious side effects from taking pain relievers or fever reducers

Ask a doctor or pharmacist before use if you are

_ taking any other drug

_ under a doctor's care for any serious condition

_ taking aspirin for heart attack or stroke, because ibuprofen may decrease this benefit of aspirin

When using this product

_ take with food or milk if stomach upset occurs

_ the risk of heart attack or stroke may increase if you use more than directed or for longer than directed

Stop use and ask a doctor if

_ you experience any of the following signs of

Drug Facts (continued)

stomach bleeding:

_ feel faint

_ have stomach pain that does not get better

_ have bloody or black stools

_ vomit blood

_ pain gets worse or lasts more than 10 days

_ fever gets worse or lasts more than 3 days

_ redness or swelling is present in the painful area

_ any new symptoms appear

If pregnant or breast-feeding,

ask a health professional before use. It is especially important not to use ibuprofen during the last 3 months of pregnancy unless definitely directed to do so by a doctor because it may cause problems in the unborn child or complications during delivery.

Keep out of reach of children.

In case of overdose, get medical help or contact a Poison Control Center right away. (1-800-222-1222)

Drug Facts (continued)

Directions

_ do not take more than directed

_ the smallest effective dose should be used

_ adults and children 12 years and over: take 1 capsule every 4 to 6 hours while symptoms persist

_ if pain or fever does not respond to 1 capsule, 2 capsules may be used

_ do not exceed 6 capsules in 24 hours, unless directed by a doctor

_ children under 12 years: ask a doctor

Other information

_ each capsule contains: potassium 28 mg

_ read all warnings and directions before use.

_ store at 20°-25°C (68°-77°F)

_ avoid excessive heat above 40°C (104°F)

Drug Facts (continued)

Inactive ingredients

FD&C green #3, gelatin, isopropyl alcohol, medium chain triglycerides, polyethylene glycol, potassium hydroxide, purified water, sorbitol special, and white edible ink

Questions or comments?

1-800-901-2420

Product of China

PRINCIPAL DISPLAY PANEL

b+b
better by giving
IBUPROFEN
SOFTGELS
20 Softgels
(200 mg each)

PRINCIPAL DISPLAY PANEL

b+b
better by giving
IBUPROFEN
SOFTGELS
40 Softgels
(200 mg each)

PRINCIPAL DISPLAY PANEL

NDC 70729-509-32
b+b
IBUPROFEN
SOFTGELS
120 Softgels
(200 mg each)